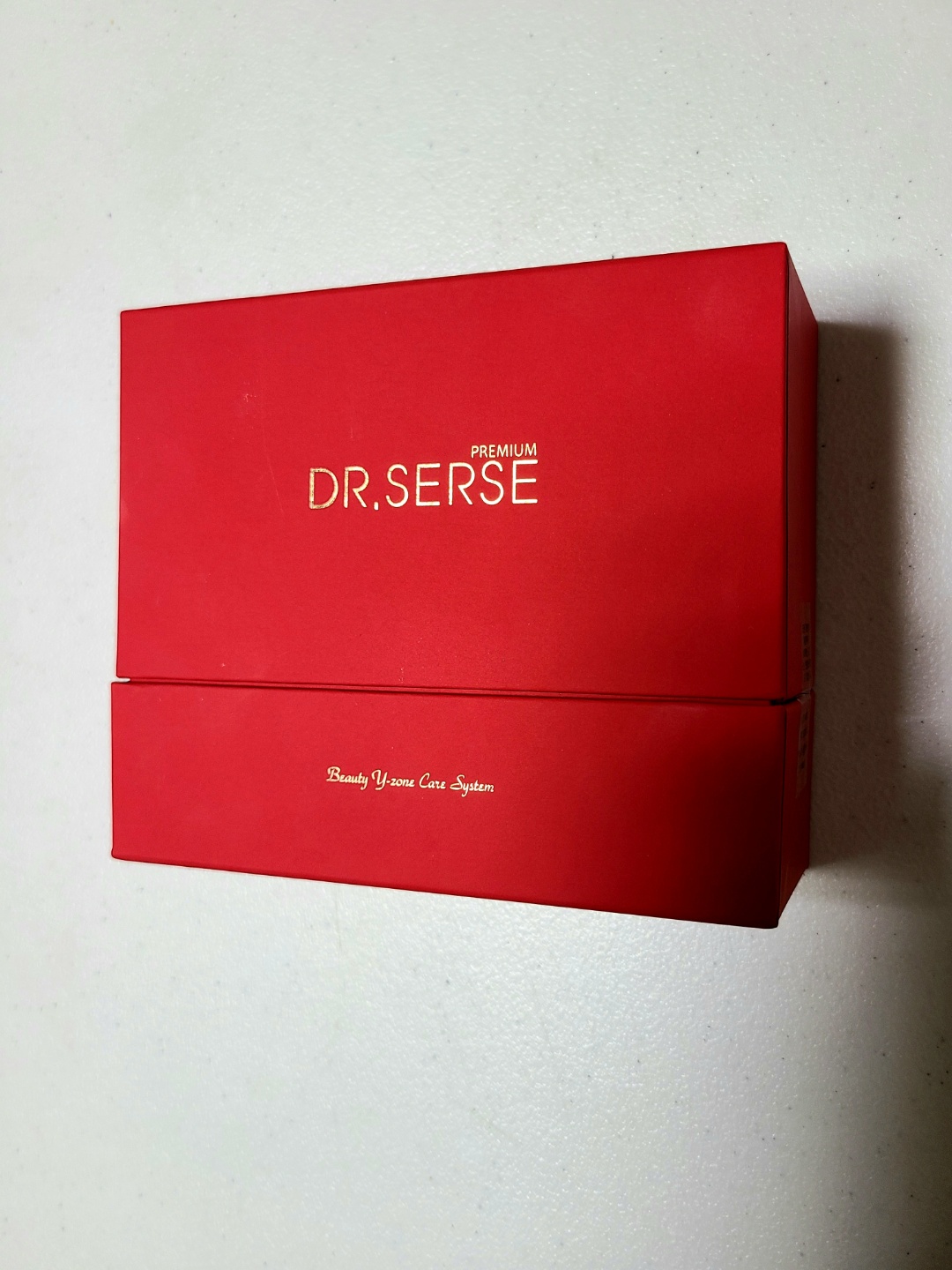 DRUG LABEL: DR.SERSE Serum
NDC: 71540-0002 | Form: GEL
Manufacturer: T.S international
Category: otc | Type: HUMAN OTC DRUG LABEL
Date: 20210607

ACTIVE INGREDIENTS: GLYCERIN 1 g/100 mL
INACTIVE INGREDIENTS: WATER; HUMAN ADIPOSE; BUTYLENE GLYCOL

Drug Facts

ACTIVE INGREDIENT

GLYCERIN

INACTIVE INGREDIENT

Human Adipose Stromal Cell Conditioned Media, Water, 1,2-Hexanediol, Xanthan Gum, Cellulose, Hydroxyethyl Acrylate/Sodium Acryloyldimethyl Taurate Copolymer, Polyglyceryl-10 Laurate, Polyglyceryl-10 Myristate, Lactobacillus Ferment, Butylene Glycol, Ethylhexylglycerin, Allantoin, Algin, Tromethamine, Hydrogenated Lecithin, Sodium Acetate, Citric Acid, Menthol, Disodium EDTA, Polysorbate 60, Sorbitan Isostearate, Lactic Acid, Lavandula Angustifolia (Lavender) Oil, 3-O-Ethyl Ascorbic Acid, Hydroxyethylcellulose, Artemisia Capillaris Leaf Extract, Simmondsia Chinensis (Jojoba) Seed Oil, Squalane, Sophora Angustifolia Root Extract, Collagen Extract, Copper Tripeptide-1, Acetyl Hexapeptide-8, rh-Polypeptide-1, rh-Oligopeptide-2, rh-Oligopeptide-1, Linalool

PURPOSE

Skin protectant

keep out of reach of the children

INDICATIONS AND USAGE

1.Take out appropriate amount of this serum on the hand
2.spread it evenly on the skin.
3.Massage gently in the skin.
4.fully absorbs the product.

WARNINGS

•Precautions when using

1. After using or using cosmetics, consult a specialist if you have any abnormal symptoms such as red spots, swelling or itching or side effects caused by direct sunlight.

2. Do not use on wounded area

3. storage and handling Precautions

a) Keep out of the reach of children

b) Store away from direct sunlight.

DOSAGE AND ADMINISTRATION

for external use only